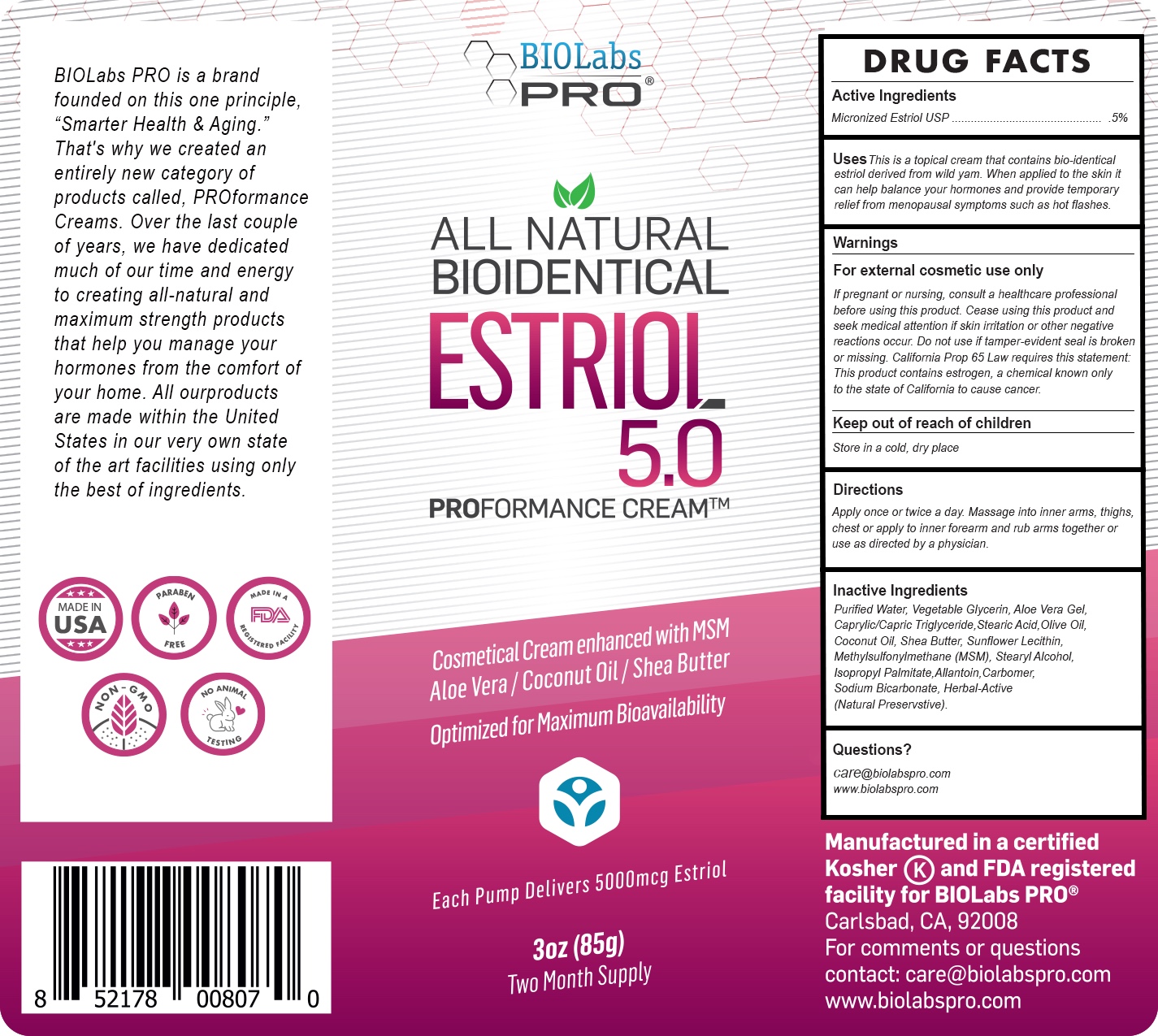 DRUG LABEL: Estriol 5.0 Cream
NDC: 82018-0010 | Form: CREAM
Manufacturer: SHYNE BRANDS
Category: otc | Type: HUMAN OTC DRUG LABEL
Date: 20250601

ACTIVE INGREDIENTS: ESTRIOL 5 mg/85 g
INACTIVE INGREDIENTS: STEARIC ACID 1 mg/85 g; ALLANTOIN 1 mg/85 g; LECITHIN, SUNFLOWER 1 mg/85 g; SHEA BUTTER 1 mg/85 g; COCONUT OIL 1 mg/85 g; ALOE VERA LEAF 1 mg/85 g; OLIVE OIL 1 mg/85 g; SODIUM BICARBONATE 1 mg/85 g; ISOPROPYL PALMITATE 1 mg/85 g; GLYCERIN 1 mg/85 g

Estriol 5.0 Cream

DRUG FACTS

Active Ingredients

Micronizrd Estriol USP (Wild Yam) .5%

PURPOSE

This is a topical cream that contains bio-identical estriol derived from wild yam. When applied to the skin it can help balance your hormones and provide temporary relief from menopausal symptoms such as hot flashes

USES:

This is a topical cream that contains bio-identical estriol derived from wild yam. When applied to the skin it can help balance your hormones and provide temporary relief from menopausal symptoms such as hot flashes.

DIRECTIONS:

Apply once or twice a day. Massage into inner arms, thighs, chest or apply to inner forearm and rub arms together or use as directed by your Physician.

WARNINGS

For external cosmetic use only. If pregnant or nursing, consult a healthcare professional before using this product. Cease using this product and seek medical attention if skin irritation or other negative reactions occur. Do not use if tamper-evident seal is broken or missing. California Prop 65 Law requires this statement:

This product contains estrogen, a chemical known only to the state of California to cause cancer.

KEEP OUT OF REACH OF CHILDREN.

PREGNANCY OR BREAST FEEDING

If pregnant or nursing or if you have a serious medical condition consult a healthcare professional before using this product.

Keep Out of Reach of Children.

DOSAGE AND ADMINISTRATION

Apply once or twice a day. Massage into inner arms, thighs, chest or apply to inner forearm and rub arms together or use as directed by you physician.

INACTIVE INGREDIENT

Purified Water, Vegetable Glycerin, Aloe Vera Gel,Caprylic/Capric Triglyceride,Stearic Acid,Olive Oil, Coconut Oil, Shea Butter, Sunflower Lecithin, Methylsulfonylmethane (MSM), Stearyl Alcohol,Isopropyl Palmitate,Allantoin,Carbomer,Sodium Bicarbonate, Herbal-Active® (Natural Preservative)

Questions?

care@biolabspro.com

www.biolabspro.com